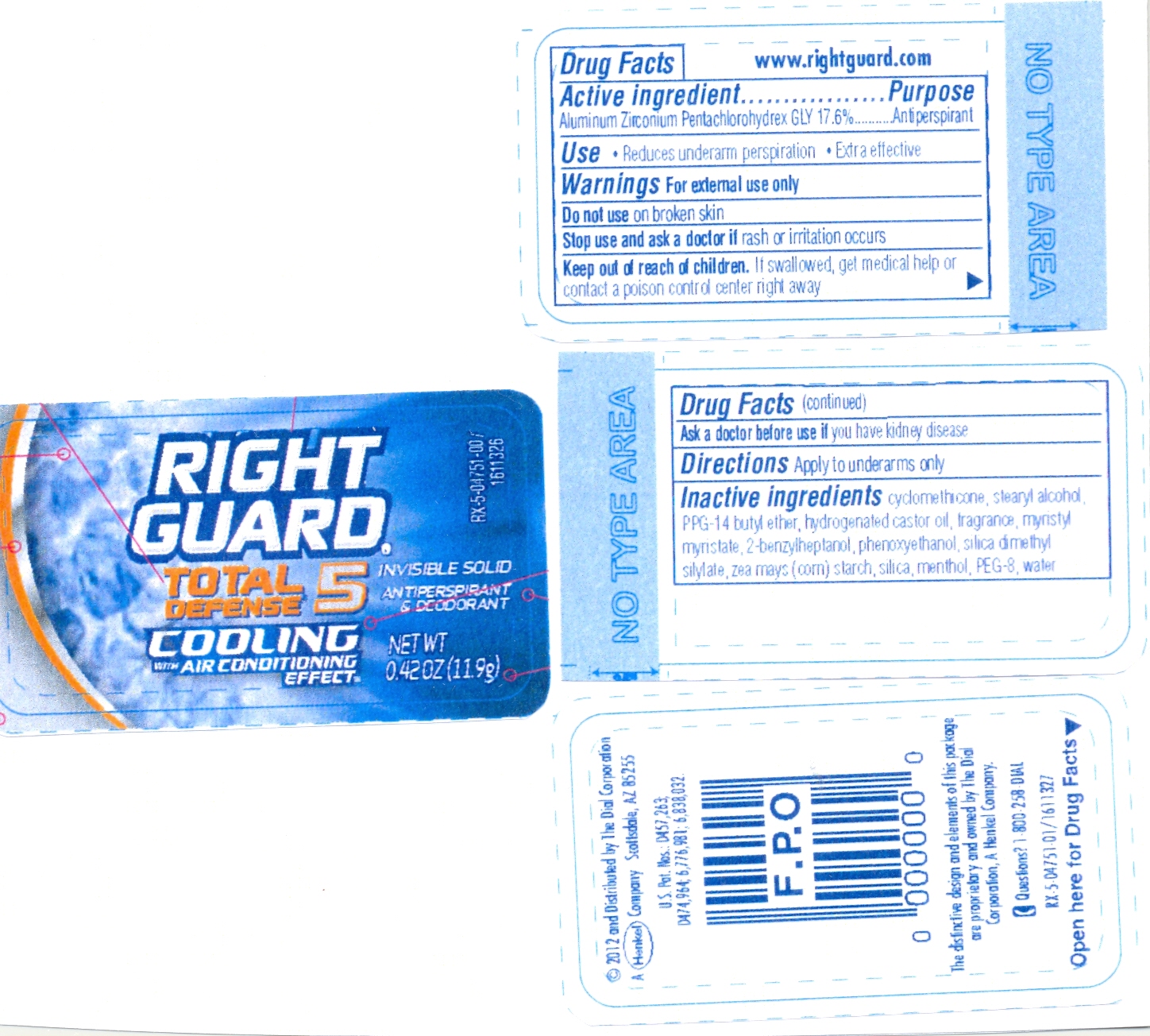 DRUG LABEL: RG TD5 Inv.Solid Antiperspirant Deodorant Cooling
NDC: 54340-011 | Form: STICK
Manufacturer: The Dial Corporation
Category: otc | Type: HUMAN OTC DRUG LABEL
Date: 20111108

ACTIVE INGREDIENTS: Aluminum Zirconium Pentachlorohydrex Gly 2.0944 g/11.9 g
INACTIVE INGREDIENTS: CYCLOMETHICONE 5 7.2018 g/11.9 g; STEARYL ALCOHOL 2.229 g/11.9 g; PPG-14 BUTYL ETHER 1.309 g/11.9 g; HYDROGENATED CASTOR OIL 0.338 g/11.9 g; MYRISTYL MYRISTATE 0.228 g/11.9 g

Right Guard Total Defense 5 Invisible Solid Antiperspirant Deodorant Cooling

ACTIVE INGREDIENT

Aluminum Zirconium Pentachlorohydrex Gly 17.8%

PURPOSE

Antiperspirant

INDICATIONS AND USAGE

Use: Reduces underarm perspiration , Extra effective

Warnings: For external use only.

Do not use on broken skin.

Stop use and ask a doctor if rash or irritation occurs.

Keep out of reach of children. If swallowed, get medical help or contact a poison control center right away.

Ask a doctor before use if you have kidney disease.

DOSAGE AND ADMINISTRATION

Directions: Apply to underarms only.

INACTIVE INGREDIENT

Cyclomethicone, stearyl alcohol, PPG-14 butyl ether, hydrogenated castor oil, fragrance, myristyl myristate, silica dimethyl silylate, zea mays (com) starch, silica, 2-benzylheptanol, phenoxyethanol.

PURPOSE

Protects 48 hours from odor, 24 hours from wetness.

HOW SUPPLIED

2011 Distributed by The Dial Corporation A Henkel Company Scottsdale, AZ, 85255. The distinctive design and elements of this package are proprietary and owned by the Dial Corporation, a Henkel Company. U.S.PAT.NO.:5,417,964

Questions? 1-800-258-DIAL, MADE IN CANADA